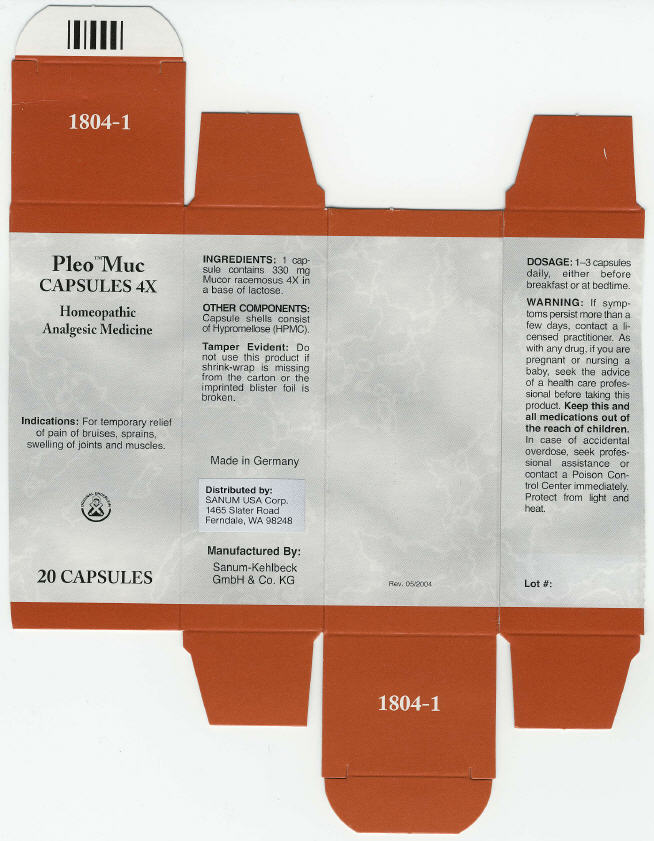 DRUG LABEL: Pleo Muc
NDC: 60681-1804 | Form: CAPSULE
Manufacturer: Sanum Kehlbeck GmbH & Co. KG
Category: homeopathic | Type: HUMAN OTC DRUG LABEL
Date: 20091014

ACTIVE INGREDIENTS: mucor racemosus 4 [HP_X]/1 1
INACTIVE INGREDIENTS: lactose

Pleo™ Muc
CAPSULES 4X

Homeopathic Analgesic Medicine

20 CAPSULES

Indications

For temporary relief of pain of bruises, sprains, swelling of joints and muscles.

INGREDIENTS

1 capsule contains 330 mg Mucor racemosus 4X in a base of lactose.

OTHER COMPONENTS

Capsule shells consist of Hypromellose (HPMC).

Tamper Evident

Do not use this product if shrink-wrap is missing from the carton or the imprinted blister foil is broken.

DOSAGE

1–3 capsules daily, either before breakfast or at bedtime.

WARNING

If symptoms persist more than a few days, contact a licensed practitioner. As with any drug, if you are pregnant or nursing a baby, seek the advice of a health care professional before taking this product.

KEEP OUT OF REACH OF CHILDREN

Keep this and all medications out of the reach of children. In case of accidental overdose, seek professional assistance or contact a Poison Control Center immediately.

STORAGE AND HANDLING

Protect from light and heat.

Made in Germany

Distributed by:
SANUM USA Corp.
1465 Slater Road
Ferndale, WA 98248

Manufactured By:
Sanum-Kehlbeck
GmbH & Co. KG

Rev. 05/2004

PRINCIPAL DISPLAY PANEL - 20 Capsule Carton

Pleo™ Muc
CAPSULES 4X

Homeopathic
Analgesic Medicine

Indications: For temporary relief
of pain of bruises, sprains,
swelling of joints and muscles.

ORIGINAL ENDERLEIN

20 CAPSULES